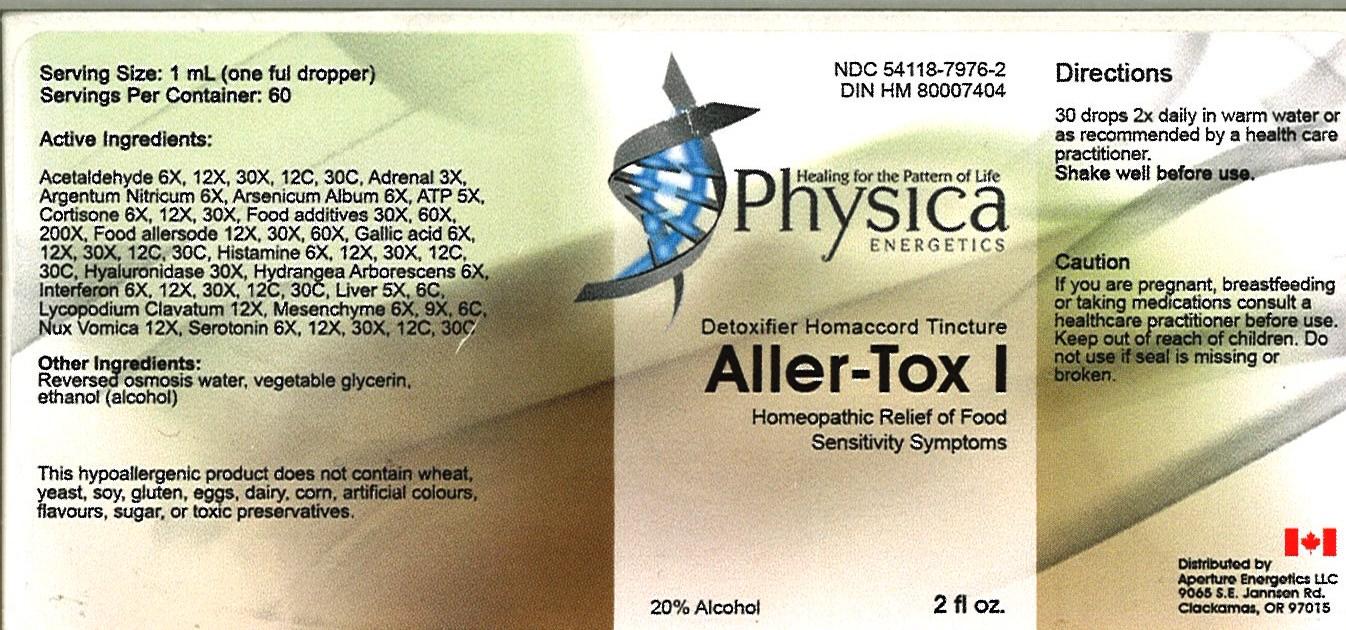 DRUG LABEL: Aller-Tox 1
NDC: 54118-7976 | Form: SOLUTION/ DROPS
Manufacturer: ABCO Laboratories, Inc.
Category: homeopathic | Type: HUMAN OTC DRUG LABEL
Date: 20121121

ACTIVE INGREDIENTS: ACETALDEHYDE 6 [hp_X]/60 mL; BOS TAURUS ADRENAL GLAND 3 [hp_X]/60 mL; SILVER NITRATE 6 [hp_X]/60 mL; ARSENIC TRIOXIDE 6 [hp_X]/60 mL; ADENOSINE TRIPHOSPHATE 5 [hp_X]/60 mL; CORTISONE 6 [hp_X]/60 mL; BERBERIS VULGARIS ROOT BARK 30 [hp_X]/60 mL; CORTICOTROPIN 12 [hp_X]/60 mL; GALLIC ACID MONOHYDRATE 6 [hp_X]/60 mL; HISTAMINE 6 [hp_X]/60 mL; HYALURONIDASE 6 [hp_X]/60 mL; INTERFERON BETA-1A 6 [hp_X]/60 mL; MAMMAL LIVER 5 [hp_X]/60 mL; LYCOPODIUM CLAVATUM SPORE 12 [hp_X]/60 mL; BOS TAURUS MESENCHYME 6 [hp_X]/60 mL; SEROTONIN 6 [hp_X]/60 mL; HYDRANGEA ARBORESCENS ROOT 6 [hp_X]/60 mL; STRYCHNOS NUX-VOMICA SEED 12 [hp_X]/60 mL
INACTIVE INGREDIENTS: WATER; GLYCERIN; ALCOHOL

Aller-Tox 1

Active Ingredients:

Acetaldehyde 6X, 12X, 30x, 12C, 30C

Adrenal 3X

Argentum Nitricum 6X

Arsenicum Album 6X

ATP 5X

Cortisone 6X, 12X, 30X

Food additives 30X, 60X, 200X

Food allersode 12X, 30X, 60X

Gallic acid 6X, 12X, 30X, 12C, 30C

Histamine 6X, 12X, 30X, 12C, 30C

Hyaluronidase 30X

Hydrangea Arborescens 6X

Interferon 6X, 12X, 30X, 12C, 30C

Liver 5X, 6C,

Lycopodium Clavatum 12X

Mesenchyme 6X, 9X, 6C

Nux Vomica 12X

Serotonin 6X, 12X, 30X, 12C, 30C

PURPOSE

- Homeopathic Relief of Food Sensitivity Symptoms

- Keep out of reach of children

INDICATIONS AND USAGE

- 30 drops 2X daily in warm water
- or as recommended by a health care practitioner

WARNINGS

- If you are pregnant, breastfeeding or taking medications consult a healthcare practitioner before use.
- Keep out of reach of children.
- Do not use if seal is missing or broken.

DOSAGE AND ADMINISTRATION

- 30 drops 2X daily
- or as recommended by a health care practitioner
- Shake well before use.

INACTIVE INGREDIENT

- Reversed osmosis water
- vegetable glycerin
- alcohol (ethanol)

PACKAGE LABEL

- aller tox.jpg
- bottle image/jpeg